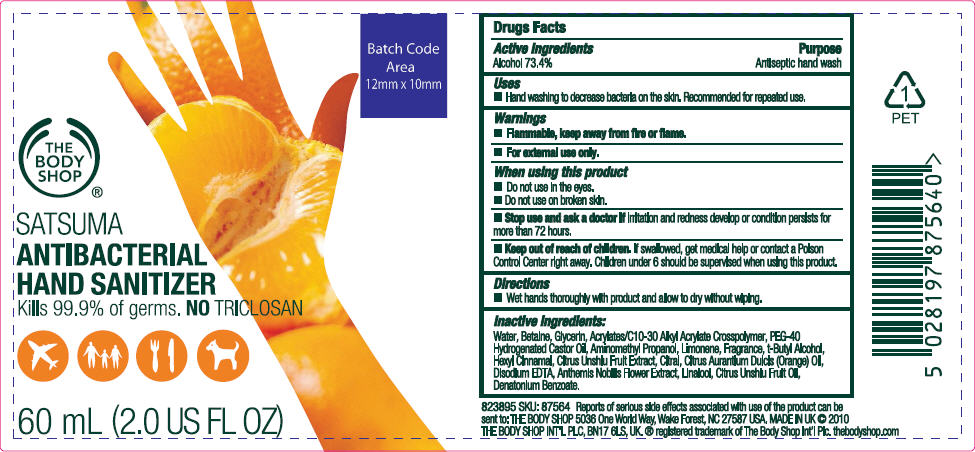 DRUG LABEL: Satsuma 
NDC: 57691-564 | Form: GEL
Manufacturer: The Body Shop Wake Forest
Category: otc | Type: HUMAN OTC DRUG LABEL
Date: 20100812

ACTIVE INGREDIENTS: Alcohol 0.734 g/1 mL
INACTIVE INGREDIENTS: Water; Betaine; Glycerin; Polyoxyl 40 Hydrogenated Castor Oil; AminomethylPropanol; .alpha.-hexylcinnamaldehyde; Tangerine; Citral; Orange Oil; Edetate Disodium; Chamaemelum Nobile Flower; Linalool, DL-; Denatonium Benzoate

SATSUMA
ANTIBACTERIAL
HAND SANITIZER

Drug Facts

Active Ingredients

Alcohol 73.4%

Purpose

Antiseptic hand wash

Uses

- Hand washing to decrease bacteria on the skin. Recommended for repeated use.

Warnings

- Flammable, keep away from fire or flame.
- For external use only.

When using this product

- Do not use in the eyes.
- Do not use on broken skin.

- Stop use and ask a doctor if irritation and redness develop or condition persists for more than 72 hours.

- Keep out of reach of children. If swallowed, get medical help or contact a Poison Control Center right away. Children under 6 should be supervised when using this product.

Directions

- Wet hands thoroughly with product and allow to dry without wiping.

Inactive ingredients

Water, Betaine, Glycerin, Acrylates/C10-30 Alkyl Acrylate Crosspolymer, PEG-40 Hydrogenated Castor Oil, Aminomethyl Propanol, Limonene, Fragrance, t-Butyl Alcohol, Hexyl Cinnamal, Citrus Unshiu Fruit Extract, Citral, Citrus Aurantium Dulcis (Orange) Oil, Disodium EDTA, Anthemis Nobilis Flower Extract, Linalool, Citrus Unshiu Fruit Oil, Denatonium Benzoate.

PRINCIPAL DISPLAY PANEL - 60 mL Bottle Label

THE
BODY
SHOP®

SATSUMA
ANTIBACTERIAL
HAND SANITIZER
Kills 99.9% of germs. NO TRICLOSAN

60 mL (2.0 US FL OZ)